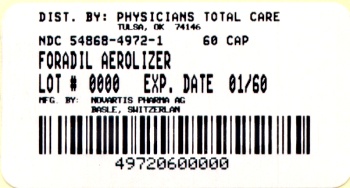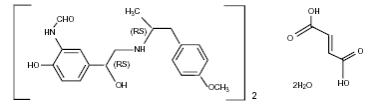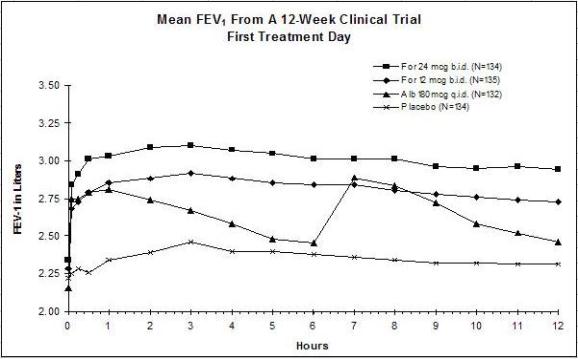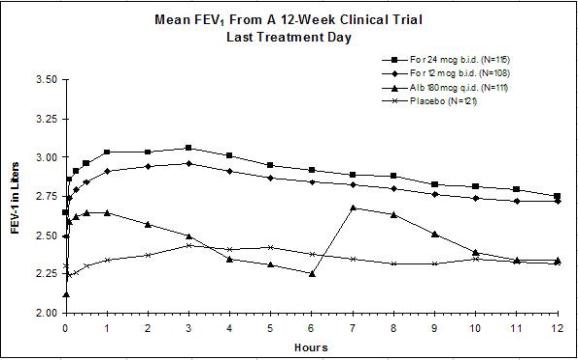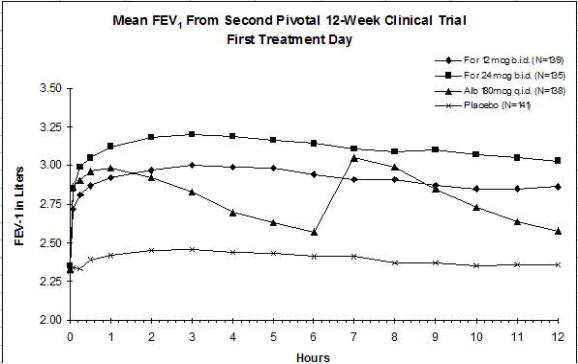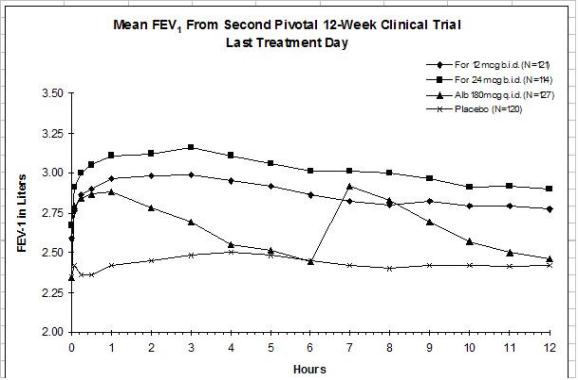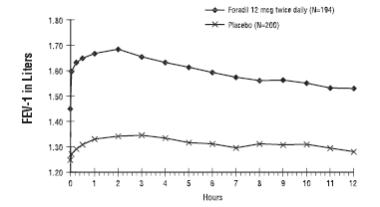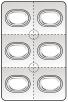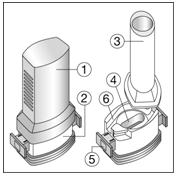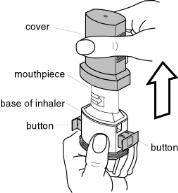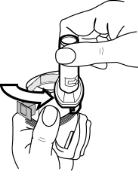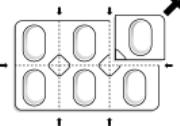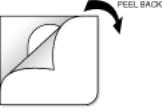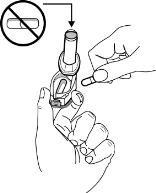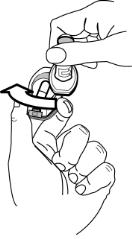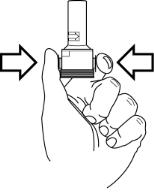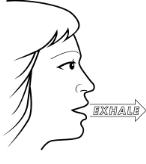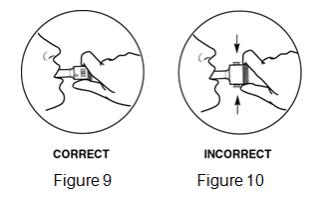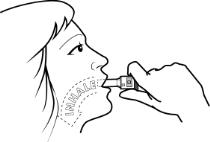 DRUG LABEL: Foradil
NDC: 54868-4972 | Form: CAPSULE
Manufacturer: Physicians Total Care, Inc.
Category: prescription | Type: HUMAN PRESCRIPTION DRUG LABEL
Date: 20120301

ACTIVE INGREDIENTS: FORMOTEROL FUMARATE 12 ug/1 1
INACTIVE INGREDIENTS: LACTOSE 25 mg/1 1

Foradil

FORADIL® AEROLIZER®

(formoterol fumarate inhalation powder)

For Oral Inhalation Only

Rx only

Prescribing Information

WARNING: ASTHMA RELATED DEATH

Long-acting beta 2-adrenergic agonists (LABA), such as formoterol the active ingredient in FORADIL AEROLIZER, increase the risk of asthma-related death. Data from a large placebo-controlled US study that compared the safety of another LABA (salmeterol) or placebo added to usual asthma therapy showed an increase in asthma-related deaths in patients receiving salmeterol. This finding with salmeterol is considered a class effect of LABA, including formoterol (see WARNINGS). Currently available data are inadequate to determine whether concurrent use of inhaled corticosteroids or other long-term asthma control drugs mitigates the increased risk of asthma-related death from LABA.

Because of this risk, use of FORADIL AEROLIZER for the treatment of asthma without a concomitant long-term asthma control medication, such as an inhaled corticosteroid, is contraindicated. Use FORADIL AEROLIZER only as additional therapy for patients with asthma who are currently taking but are inadequately controlled on a long-term asthma control medication, such as an inhaled corticosteroid. Once asthma control is achieved and maintained, assess the patient at regular intervals and step down therapy (e.g. discontinue FORADIL AEROLIZER) if possible without loss of asthma control, and maintain the patient on a long-term asthma control medication, such as an inhaled corticosteroid. Do not use FORADIL AEROLIZER for patients whose asthma is adequately controlled on low or medium dose inhaled corticosteroids.

Pediatric and Adolescent Patients

Available data from controlled clinical trials suggest that LABA increase the risk of asthma-related hospitalization in pediatric and adolescent patients. For pediatric and adolescent patients with asthma who require addition of a LABA to an inhaled corticosteroid, a fixed-dose combination product containing both an inhaled corticosteroid and LABA should ordinarily be considered to ensure adherence with both drugs. In cases where use of a separate long-term asthma control medication (e.g. inhaled corticosteroid) and LABA is clinically indicated, appropriate steps must be taken to ensure adherence with both treatment components. If adherence cannot be assured, a fixed-dose combination product containing both an inhaled corticosteroid and LABA is recommended.

DESCRIPTION

FORADIL® AEROLIZER® consists of a capsule dosage form containing a dry powder formulation of FORADIL (formoterol fumarate) intended for oral inhalation only with the AEROLIZER Inhaler.

Each clear, hard gelatin capsule contains a dry powder blend of 12 mcg of formoterol fumarate and 25 mg of lactose (which contains trace levels of milk proteins) as a carrier.

The active component of FORADIL is formoterol fumarate, a racemate. Formoterol fumarate is a selective beta2-adrenergic bronchodilator. Its chemical name is (±)-2-hydroxy-5-[(1RS)-1-hydroxy-2-[[(1RS)-2-(4-methoxyphenyl)-1-methylethyl]-amino]ethyl]formanilide fumarate dihydrate; its structural formula is

Formoterol fumarate has a molecular weight of 840.9, and its empirical formula is (C19H24N2O4)2•C4H4O4•2H2O. Formoterol fumarate is a white to yellowish crystalline powder, which is freely soluble in glacial acetic acid, soluble in methanol, sparingly soluble in ethanol and isopropanol, slightly soluble in water, and practically insoluble in acetone, ethyl acetate, and diethyl ether.

The AEROLIZER Inhaler is a plastic device used for inhaling FORADIL. The amount of drug delivered to the lung will depend on patient factors, such as inspiratory flow rate and inspiratory time. Under standardized in vitro testing at a fixed flow rate of 60 L/min for 2 seconds, the AEROLIZER Inhaler delivered 10 mcg of formoterol fumarate from the mouthpiece. Peak inspiratory flow rates (PIFR) achievable through the AEROLIZER Inhaler were evaluated in 33 adult and adolescent patients and 32 pediatric patients with mild-to-moderate asthma. Mean PIFR was 117.82 L/min (range 34-188 L/min) for adult and adolescent patients, and 99.66 L/min (range 43-187 L/min) for pediatric patients. Approximately ninety percent of each population studied generated a PIFR through the device exceeding 60 L/min.

To use the delivery system, a FORADIL capsule is placed in the well of the AEROLIZER Inhaler, and the capsule is pierced by pressing and releasing the buttons on the side of the device. The formoterol fumarate formulation is dispersed into the air stream when the patient inhales rapidly and deeply through the mouthpiece.

CLINICAL PHARMACOLOGY

Mechanism of Action

Formoterol fumarate is a long-acting selective beta2-adrenergic receptor agonist (beta2-agonist). Inhaled formoterol fumarate acts locally in the lung as a bronchodilator. In vitro studies have shown that formoterol has more than 200-fold greater agonist activity at beta2-receptors than at beta1-receptors. Although beta2-receptors are the predominant adrenergic receptors in bronchial smooth muscle and beta1-receptors are the predominant receptors in the heart, there are also beta2-receptors in the human heart comprising 10%-50% of the total beta-adrenergic receptors. The precise function of these receptors has not been established, but they raise the possibility that even highly selective beta2-agonists may have cardiac effects.

The pharmacologic effects of beta2-adrenoceptor agonist drugs, including formoterol, are at least in part attributable to stimulation of intracellular adenyl cyclase, the enzyme that catalyzes the conversion of adenosine triphosphate (ATP) to cyclic-3', 5'-adenosine monophosphate (cyclic AMP). Increased cyclic AMP levels cause relaxation of bronchial smooth muscle and inhibition of release of mediators of immediate hypersensitivity from cells, especially from mast cells.

In vitro tests show that formoterol is an inhibitor of the release of mast cell mediators, such as histamine and leukotrienes, from the human lung. Formoterol also inhibits histamine-induced plasma albumin extravasation in anesthetized guinea pigs and inhibits allergen-induced eosinophil influx in dogs with airway hyper-responsiveness. The relevance of these in vitro and animal findings to humans is unknown.

Animal Pharmacology

Studies in laboratory animals (minipigs, rodents, and dogs) have demonstrated the occurrence of cardiac arrhythmias and sudden death (with histologic evidence of myocardial necrosis) when beta-agonists and methylxanthines are administered concurrently. The clinical significance of these findings is unknown.

Pharmacokinetics

Information on the pharmacokinetics of formoterol in plasma has been obtained in healthy subjects by oral inhalation of doses higher than the recommended range and in Chronic Obstructive Pulmonary Disease (COPD) patients after oral inhalation of doses at and above the therapeutic dose. Urinary excretion of unchanged formoterol was used as an indirect measure of systemic exposure. Plasma drug disposition data parallel urinary excretion, and the elimination half-lives calculated for urine and plasma are similar.

Absorption

Following inhalation of a single 120 mcg dose of formoterol fumarate by 12 healthy subjects, formoterol was rapidly absorbed into plasma, reaching a maximum drug concentration of 92 pg/mL within 5 minutes of dosing. In COPD patients treated for 12 weeks with formoterol fumarate 12 or 24 mcg b.i.d., the mean plasma concentrations of formoterol ranged between 4.0 and 8.8 pg/mL and 8.0 and 17.3 pg/mL, respectively, at 10 min, 2 h and 6 h post inhalation.

Following inhalation of 12 to 96 mcg of formoterol fumarate by 10 healthy males, urinary excretion of both (R,R)- and (S,S)-enantiomers of formoterol increased proportionally to the dose. Thus, absorption of formoterol following inhalation appeared linear over the dose range studied.

In a study in patients with asthma, when formoterol 12 or 24 mcg twice daily was given by oral inhalation for 4 weeks or 12 weeks, the accumulation index, based on the urinary excretion of unchanged formoterol ranged from 1.63 to 2.08 in comparison with the first dose. For COPD patients, when formoterol 12 or 24 mcg twice daily was given by oral inhalation for 12 weeks, the accumulation index, based on the urinary excretion of unchanged formoterol was 1.19 - 1.38. This suggests some accumulation of formoterol in plasma with multiple dosing. The excreted amounts of formoterol at steady-state were close to those predicted based on single-dose kinetics. As with many drug products for oral inhalation, it is likely that the majority of the inhaled formoterol fumarate delivered is swallowed and then absorbed from the gastrointestinal tract.

Distribution

The binding of formoterol to human plasma proteins in vitro was 61%-64% at concentrations from 0.1 to 100 ng/mL. Binding to human serum albumin in vitro was 31%-38% over a range of 5 to 500 ng/mL. The concentrations of formoterol used to assess the plasma protein binding were higher than those achieved in plasma following inhalation of a single 120 mcg dose.

Metabolism

Formoterol is metabolized primarily by direct glucuronidation at either the phenolic or aliphatic hydroxyl group and O-demethylation followed by glucuronide conjugation at either phenolic hydroxyl groups. Minor pathways involve sulfate conjugation of formoterol and deformylation followed by sulfate conjugation. The most prominent pathway involves direct conjugation at the phenolic hydroxyl group. The second major pathway involves O-demethylation followed by conjugation at the phenolic 2'-hydroxyl group. Four cytochrome P450 isozymes (CYP2D6, CYP2C19, CYP2C9 and CYP2A6) are involved in the O-demethylation of formoterol. Formoterol did not inhibit CYP450 enzymes at therapeutically relevant concentrations. Some patients may be deficient in CYP2D6 or 2C19 or both. Whether a deficiency in one or both of these isozymes results in elevated systemic exposure to formoterol or systemic adverse effects has not been adequately explored.

Excretion

Following oral administration of 80 mcg of radiolabeled formoterol fumarate to 2 healthy subjects, 59%-62% of the radioactivity was eliminated in the urine and 32%-34% in the feces over a period of 104 hours. Renal clearance of formoterol from blood in these subjects was about 150 mL/min. Following inhalation of a 12 mcg or 24 mcg dose by 16 patients with asthma, about 10% and 15%-18% of the total dose was excreted in the urine as unchanged formoterol and direct conjugates of formoterol, respectively. Following inhalation of 12 mcg or 24 mcg dose by 18 patients with COPD the corresponding values were 7% and 6-9% of the dose, respectively.

Based on plasma concentrations measured following inhalation of a single 120 mcg dose by 12 healthy subjects, the mean terminal elimination half-life was determined to be 10 hours. From urinary excretion rates measured in these subjects, the mean terminal elimination half-lives for the (R,R)- and (S,S)-enantiomers were determined to be 13.9 and 12.3 hours, respectively. The (R,R)- and (S,S)-enantiomers represented about 40% and 60% of unchanged drug excreted in the urine, respectively, following single inhaled doses between 12 and 120 mcg in healthy volunteers and single and repeated doses of 12 and 24 mcg in patients with asthma. Thus, the relative proportion of the two enantiomers remained constant over the dose range studied and there was no evidence of relative accumulation of one enantiomer over the other after repeated dosing.

Special Populations

Gender: After correction for body weight, formoterol pharmacokinetics did not differ significantly between males and females.

Geriatric and Pediatric: The pharmacokinetics of formoterol have not been studied in the elderly population, and limited data are available in pediatric patients.

In a study of children with asthma who were 5 to 12 years of age, when formoterol fumarate 12 or 24 mcg was given twice daily by oral inhalation for 12 weeks, the accumulation index ranged from 1.18 to 1.84 based on urinary excretion of unchanged formoterol. Hence, the accumulation in children did not exceed that in adults, where the accumulation index ranged from 1.63 to 2.08 (see above). Approximately 6% and 6.5% to 9% of the dose was recovered in the urine of the children as unchanged and conjugated formoterol, respectively.

Hepatic/Renal Impairment: The pharmacokinetics of formoterol have not been studied in subjects with hepatic or renal impairment.

Pharmacodynamics

Systemic Safety and Pharmacokinetic/Pharmacodynamic Relationships

The major adverse effects of inhaled beta2-agonists occur as a result of excessive activation of the systemic beta-adrenergic receptors. The most common adverse effects in adults and adolescents include skeletal muscle tremor and cramps, insomnia, tachycardia, decreases in plasma potassium, and increases in plasma glucose.

Pharmacokinetic/pharmacodynamic (PK/PD) relationships between heart rate, ECG parameters, and serum potassium levels and the urinary excretion of formoterol were evaluated in 10 healthy male volunteers (25 to 45 years of age) following inhalation of single doses containing 12, 24, 48, or 96 mcg of formoterol fumarate. There was a linear relationship between urinary formoterol excretion and decreases in serum potassium, increases in plasma glucose, and increases in heart rate.

In a second study, PK/PD relationships between plasma formoterol levels and pulse rate, ECG parameters, and plasma potassium levels were evaluated in 12 healthy volunteers following inhalation of a single 120 mcg dose of formoterol fumarate (10 times the recommended clinical dose). Reductions of plasma potassium concentration were observed in all subjects. Maximum reductions from baseline ranged from 0.55 to 1.52 mmol/L with a median maximum reduction of 1.01 mmol/L. The formoterol plasma concentration was highly correlated with the reduction in plasma potassium concentration. Generally, the maximum effect on plasma potassium was noted 1 to 3 hours after peak formoterol plasma concentrations were achieved. A mean maximum increase of pulse rate of 26 bpm was observed 6 hours post dose. The maximum increase of mean corrected QT interval (QTc) was 25 msec when calculated using Bazett's correction and was 8 msec when calculated using Fridericia's correction. The QTc returned to baseline within 12-24 hours post-dose. Formoterol plasma concentrations were weakly correlated with pulse rate and increase of QTc duration. The effects on plasma potassium, pulse rate, and QTc interval are known pharmacological effects of this class of study drug and were not unexpected at the very high formoterol dose (120 mcg single dose, 10 times the recommended single dose) tested in this study. These effects were well-tolerated by the healthy volunteers.

The electrocardiographic and cardiovascular effects of FORADIL AEROLIZER were compared with those of albuterol and placebo in two pivotal 12-week double-blind studies of patients with asthma. A subset of patients underwent continuous electrocardiographic monitoring during three 24-hour periods. No important differences in ventricular or supraventricular ectopy between treatment groups were observed. In these two studies, the total number of patients with asthma exposed to any dose of FORADIL AEROLIZER who had continuous electrocardiographic monitoring was about 200.

Continuous electrocardiographic monitoring was performed in an 8-week, randomized, double-blind, placebo controlled trial in 204 COPD patients treated with FORADIL AEROLIZER 12 mcg twice daily or placebo. Holter monitoring was used to evaluate predefined proarrhythmic events. Non-sustained ventricular tachycardia occurred in 2 (2.2%) of FORADIL AEROLIZER treated patients compared to none in the placebo group. An increase in ventricular premature beats (VPB) occurred in 3 (3.3 %) of FORADIL AEROLIZER treated patients compared to 2 (1.9%) in the placebo group. There were no events of sustained of ventricular tachycardia, ventricular flutter or fibrillation, or symptomatic runs of VPB. One patient in the FORADIL AEROLIZER group had a serious adverse event of atrial flutter.

The electrocardiographic effects of FORADIL AEROLIZER were evaluated versus placebo in a 12-month pivotal double-blind study of patients with COPD. An analysis of ECG intervals was performed for patients who participated at study sites in the United States, including 46 patients treated with FORADIL AEROLIZER 12 mcg twice daily, and 50 patients treated with FORADIL AEROLIZER 24 mcg twice daily. ECGs were performed predose, and at 5-15 minutes and 2 hours post-dose at study baseline and after 3, 6 and 12 months of treatment. The results showed that there was no clinically meaningful acute or chronic effect on ECG intervals, including QTc, resulting from treatment with FORADIL AEROLIZER.

Tachyphylaxis/Tolerance

In a clinical study in 19 adult patients with mild asthma, the bronchoprotective effect of formoterol, as assessed by methacholine challenge, was studied following an initial dose of 24 mcg (twice the recommended dose) and after 2 weeks of 24 mcg twice daily. Tolerance to the bronchoprotective effects of formoterol was observed as evidenced by a diminished bronchoprotective effect on FEV1 after 2 weeks of dosing, with loss of protection at the end of the 12 hour dosing period.

Rebound bronchial hyper-responsiveness after cessation of chronic formoterol therapy has not been observed.

In three large clinical trials in patients with asthma, while efficacy of formoterol versus placebo was maintained, a slightly reduced bronchodilatory response (as measured by 12-hour FEV1 AUC) was observed within the formoterol arms over time, particularly with the 24 mcg twice daily dose (twice the daily recommended dose). A similarly reduced FEV1 AUC over time was also noted in the albuterol treatment arms (180 mcg four times daily by metered-dose inhaler).

CLINICAL TRIALS

Adolescent and Adult Asthma Trials

In a placebo-controlled, single-dose clinical trial, the onset of bronchodilation (defined as a 15% or greater increase from baseline in FEV1) was similar for FORADIL AEROLIZER and albuterol 180 mcg by metered-dose inhaler.

In single-dose and multiple-dose clinical trials, the maximum improvement in FEV1 for FORADIL AEROLIZER 12 mcg generally occurred within 1 to 3 hours, and an increase in FEV1 above baseline was observed for 12 hours in most patients.

FORADIL AEROLIZER 12 mcg twice daily was compared to FORADIL AEROLIZER 24 mcg twice daily, albuterol 180 mcg four times daily by metered-dose inhaler, and placebo in a total of 1095 adult and adolescent patients 12 years of age and above with mild-to-moderate asthma (defined as FEV1 40%-80% of the patient's predicted normal value) who participated in two pivotal, 12-week, multi-center, randomized, double-blind, parallel group studies.

The results of both studies showed that FORADIL AEROLIZER 12 mcg twice daily resulted in significantly greater post-dose bronchodilation (as measured by serial FEV1 for 12 hours post-dose) throughout the 12-week treatment period. There was no significant difference in post-dose bronchodilation between FORADIL AEROLIZER 12 mcg twice daily and FORADIL AEROLIZER 24 mcg twice daily, but serious asthma exacerbations occurred more commonly in the higher dose group (see WARNINGS and ADVERSE REACTIONS). Mean FEV1 measurements from both studies are shown below for the first and last treatment days (see Figures 1 and 2).

Figures 1a and 1b: Mean FEV1 from Clinical Trial A
Figures 1a and 1b: Mean FEV1 from Clinical Trial A
Figures 2a and 2b: Mean FEV1 from Clinical Trial B
Figures 2a and 2b: Mean FEV1 from Clinical Trial B

Compared with placebo and albuterol, patients treated with FORADIL AEROLIZER 12 mcg demonstrated improvement in many secondary efficacy endpoints, including improved combined and nocturnal asthma symptom scores, fewer nighttime awakenings, fewer nights in which patients used rescue medication, and higher morning and evening peak flow rates. FORADIL AEROLIZER 24 mcg twice daily did not provide any additional improvements in these secondary endpoints compared to FORADIL AEROLIZER 12 mcg twice daily.

A 16-week, randomized, multi-center, double-blind, parallel-group study enrolled 1568 patients 12 years of age and older with mild-to-moderate asthma (defined as FEV1 ≥40% of the patient’s predicted normal value) in three treatment groups: FORADIL AEROLIZER 12 mcg twice daily, FORADIL AEROLIZER 24 mcg twice daily, and placebo. The study’s primary endpoint was the incidence of serious asthma-related adverse events. Serious asthma exacerbations occurred in 3 (0.6%) patients who received FORADIL AEROLIZER 12 mcg twice daily, 2 (0.4%) patients who received FORADIL AEROLIZER 24 mcg twice daily, and 1 (0.2%) patient who received placebo. The size of this study was not adequate to precisely quantify the differences in serious asthma exacerbation rates between treatment groups. All serious asthma exacerbations resulted in hospitalizations. While there were no deaths in the study, the duration and size of this study were not adequate to quantify the rate of asthma-related death. See WARNINGS for information about a study which compared another long-acting beta2-adrenergic agonist to placebo.

Pediatric Asthma Trial

A 12-month, multi-center, randomized, double-blind, parallel-group, study compared FORADIL AEROLIZER 12 mcg twice daily and FORADIL AEROLIZER 24 mcg twice daily to placebo in a total of 518 children with asthma (ages 5-12 years) who required daily bronchodilators and anti-inflammatory treatment. Efficacy was evaluated on the first day of treatment, at Week 12, and at the end of treatment.

FORADIL AEROLIZER 12 mcg twice daily demonstrated a greater 12-hour FEV1 AUC compared to placebo on the first day of treatment, after twelve weeks of treatment, and after one year of treatment. FORADIL AEROLIZER 24 mcg twice daily did not result in any additional improvement in 12-hour FEV1 AUC compared to FORADIL AEROLIZER 12 mcg twice daily.

Exercise-Induced Bronchospasm Trials

The effect of FORADIL AEROLIZER on exercise-induced bronchospasm (defined as >20% fall in FEV1) was examined in four randomized, single-dose, double-blind, crossover studies in a total of 77 patients 4 to 41 years of age with exercise-induced bronchospasm. Exercise challenge testing was conducted 15 minutes, and 4, 8, and 12 hours following administration of a single dose of study drug (FORADIL AEROLIZER 12 mcg, albuterol 180 mcg by metered-dose inhaler, or placebo) on separate test days. FORADIL AEROLIZER 12 mcg and albuterol 180 mcg were each superior to placebo for FEV1 measurements obtained 15 minutes after study drug administration. FORADIL AEROLIZER 12 mcg maintained superiority over placebo at 4, 8, and 12 hours after administration. Most subjects were protected from exercise-induced bronchospasm for up to 12 hours following administration of FORADIL AEROLIZER; however, some were not. The efficacy of FORADIL AEROLIZER in the prevention of exercise-induced bronchospasm when dosed on a regular twice daily regimen has not been studied.

Adult COPD Trials

In multiple-dose clinical trials in patients with COPD, FORADIL AEROLIZER 12 mcg was shown to provide onset of significant bronchodilation (defined as 15% or greater increase from baseline in FEV1) within 5 minutes of oral inhalation after the first dose. Bronchodilation was maintained for at least 12 hours.

FORADIL AEROLIZER was studied in two pivotal, double-blind, placebo-controlled, randomized, multi-center, parallel-group trials in a total of 1634 adult patients (age range: 34-88 years; mean age: 63 years) with COPD who had a mean FEV1 that was 46% of predicted. The diagnosis of COPD was based upon a prior clinical diagnosis of COPD, a smoking history (greater than 10 pack-years), age (at least 40 years), spirometry results (prebronchodilator baseline FEV1 less than 70% of the predicted value, and at least 0.75 liters, with the FEV1/VC being less than 88% for men and less than 89% for women), and symptom score (greater than zero on at least four of the seven days prior to randomization). These studies included approximately equal numbers of patients with and without baseline bronchodilator reversibility, defined as a 15% or greater increase FEV1 after inhalation of 200 mcg of albuterol sulfate. A total of 405 patients received FORADIL AEROLIZER 12 mcg, administered twice daily. Each trial compared FORADIL AEROLIZER 12 mcg twice daily and FORADIL AEROLIZER 24 mcg twice daily with placebo and an active control drug. The active control drug was ipratropium bromide in COPD Trial A, and slow-release theophylline in COPD Trial B (the theophylline arm in this study was open-label). The treatment period was 12 weeks in COPD Trial A, and 12 months in COPD Trial B.

The results showed that FORADIL AEROLIZER 12 mcg twice daily resulted in significantly greater post-dose bronchodilation (as measured by serial FEV1 for 12 hours post-dose; the primary efficacy analysis) compared to placebo when evaluated after 12 weeks of treatment in both trials, and after 12 months of treatment in the 12-month trial (COPD Trial B). Compared to FORADIL AEROLIZER 12 mcg twice daily, FORADIL AEROLIZER 24 mcg twice daily did not provide any additional benefit on a variety of endpoints including FEV1.

Mean FEV1 measurements after 12 weeks of treatment for one of the two major efficacy studies are shown in the figure below.

Figure 3 Mean FEV1 after 12 Weeks of treatment from COPD Trial A

FORADIL AEROLIZER 12 mcg twice daily was statistically superior to placebo at all post-dose timepoints tested (from 5 minutes to 12 hours post-dose) throughout the 12-week (COPD Trial A) and 12-month (COPD Trial B) treatment periods.

In both pivotal trials compared with placebo, patients treated with FORADIL AEROLIZER 12 mcg demonstrated improved morning pre-medication peak expiratory flow rates and took fewer puffs of rescue albuterol.

INDICATIONS AND USAGE

Asthma

FORADIL AEROLIZER is indicated for the treatment of asthma and in the prevention of bronchospasm only as concomitant therapy with a long-term asthma control medication, such as an inhaled corticosteroid, in adults and children 5 years of age and older with reversible obstructive airways disease, including patients with symptoms of nocturnal asthma.

Long-acting beta2-adrenergic agonists (LABA), such as formoterol, the active ingredient in FORADIL AEROLIZER, increase the risk of asthma-related death (see WARNINGS). Use of FORADIL AEROLIZER for the treatment of asthma without concomitant use of a long-term asthma control medication, such as an inhaled corticosteroid, is contraindicated. Use FORADIL AEROLIZER only as additional therapy for patients with asthma who are currently taking but are inadequately controlled on a long-term asthma control medication, such as an inhaled corticosteroid. Once asthma control is achieved and maintained, assess the patient at regular intervals and step down therapy (e.g. discontinue FORADIL AEROLIZER) if possible without loss of asthma control, and maintain the patient on a long-term asthma control medication, such as an inhaled corticosteroid. Do not use FORADIL AEROLIZER for patients whose asthma is adequately controlled on low or medium dose inhaled corticosteroids.

Pediatric and Adolescent Patients

Available data from controlled clinical trials suggest that LABA increase the risk of asthma-related hospitalization in pediatric and adolescent patients (see WARNINGS). For pediatric and adolescent patients with asthma who require addition of a LABA to an inhaled corticosteroid, a fixed-dose combination product containing both an inhaled corticosteroid and LABA should ordinarily be used to ensure adherence with both drugs. In cases where use of a separate long-term asthma control medication (e.g. inhaled corticosteroid) and LABA is clinically indicated, appropriate steps must be taken to ensure adherence with both treatment components. If adherence cannot be assured, a fixed-dose combination product containing both an inhaled corticosteroid and LABA is recommended.

Exercise-Induced Bronchospasm

FORADIL AEROLIZER is also indicated for the acute prevention of exercise-induced bronchospasm (EIB) in adults and children 5 years of age and older, when administered on an occasional, as-needed basis. Use of FORADIL AEROLIZER as a single agent for the prevention of exercise-induced bronchospasm may be clinically indicated in patients who do not have persistent asthma. In patients with persistent asthma, use of FORADIL AEROLIZER for the prevention of exercise-induced bronchospasm may be clinically indicated, but the treatment of asthma should include a long-term asthma control medication, such as an inhaled corticosteroid.

Chronic Obstructive Pulmonary Disease

FORADIL AEROLIZER is indicated for the long-term, twice daily (morning and evening) administration in the maintenance treatment of bronchoconstriction in patients with Chronic Obstructive Pulmonary Disease including chronic bronchitis and emphysema.

CONTRAINDICATIONS

Because of the risk of asthma-related death and hospitalization, use of FORADIL AEROLIZER for the treatment of asthma without concomitant use of a long-term asthma control medication, such as an inhaled corticosteroid, is contraindicated (see Warnings – Asthma Related Death).

FORADIL (formoterol fumarate) is contraindicated in patients with a history of hypersensitivity to formoterol fumarate or to any components of this product.

WARNINGS

ASTHMA RELATED DEATH

Long-acting beta 2-adrenergic agonists, such as formoterol, the active ingredient in FORADIL AEROLIZER, increase the risk of asthma-related death. Currently available data are inadequate to determine whether concurrent use of inhaled corticosteroids or other long-term asthma control drugs mitigates the increased risk of asthma-related death from LABA.

Because of this risk, use of FORADIL AEROLIZER for the treatment of asthma without concomitant use of a long-term asthma control medication, such as an inhaled corticosteroid, is contraindicated. Use FORADIL AEROLIZER only as additional therapy for patients with asthma who are currently taking but are inadequately controlled on a long-term asthma control medication, such as an inhaled corticosteroid. Once asthma control is achieved and maintained, assess the patient at regular intervals and step down therapy (e.g. discontinue FORADIL AEROLIZER) if possible without loss of asthma control, and maintain the patient on a long-term asthma control medication, such as an inhaled corticosteroid. Do not use FORADIL AEROLIZER for patients whose asthma is adequately controlled on low or medium dose inhaled corticosteroids.

Pediatric and Adolescent Patients

Available data from controlled clinical trials suggest that LABA increase the risk of asthma-related hospitalization in pediatric and adolescent patients. For pediatric and adolescent patients with asthma who require addition of a LABA to an inhaled corticosteroid, a fixed-dose combination product containing both an inhaled corticosteroid and LABA should ordinarily be considered to ensure adherence with both drugs. In cases where use of a separate long-term asthma control medication (e.g. inhaled corticosteroid) and LABA is clinically indicated, appropriate steps must be taken to ensure adherence with both treatment components. If adherence cannot be assured, a fixed-dose combination product containing both an inhaled corticosteroid and LABA is recommended.

A 28-week, placebo-controlled US study comparing the safety of salmeterol with placebo, each added to usual asthma therapy, showed an increase in asthma-related deaths in patients receiving salmeterol (13/13,176 in patients treated with salmeterol vs. 3/13,179 in patients treated with placebo; RR 4.37, 95% CI 1.25, 15.34). The increased risk of asthma-related death is considered a class effect of the long-acting beta2-adrenergic agonists, including formoterol. No study adequate to determine whether the rate of asthma-related death is increased with FORADIL AEROLIZER has been conducted.

Clinical studies with FORADIL AEROLIZER suggested a higher incidence of serious asthma exacerbations in patients who received FORADIL AEROLIZER than in those who received placebo (See ADVERSE REACTIONS). The sizes of these studies were not adequate to precisely quantify the differences in serious asthma exacerbation rates between treatment groups.

The studies described above enrolled patients with asthma. No studies have been conducted that were adequate to determine whether the rate of death in patients with COPD is increased by long-acting beta 2-adrenergic agonists.

- FORADIL AEROLIZER should not be initiated in patients with significantly worsening or acutely deteriorating asthma, which may be a life-threatening condition. The use of FORADIL AEROLIZER in this setting is inappropriate.
- FORADIL AEROLIZER should not be used in conjunction with an inhaled, long-acting beta 2-agonist. FORADIL AEROLIZER should not be used with other medications containing long-acting beta 2-agonists.
- FORADIL AEROLIZER is not a substitute for inhaled or oral corticosteroids. Corticosteroids should not be stopped or reduced at the time FORADIL AEROLIZER is initiated.
- When beginning treatment with FORADIL AEROLIZER, patients who have been taking inhaled, short-acting beta 2-agonists on a regular basis (e.g., four times a day) should be instructed to discontinue the regular use of these drugs and use them only for symptomatic relief of acute asthma symptoms.
- See PRECAUTIONS, Information for Patients and the accompanying Medication Guide.

Paradoxical Bronchospasm

As with other inhaled beta2-agonists, formoterol can produce paradoxical bronchospasm, that may be life-threatening. If paradoxical bronchospasm occurs, FORADIL AEROLIZER should be discontinued immediately and alternative therapy instituted.

Deterioration of Asthma

Asthma may deteriorate acutely over a period of hours or chronically over several days or longer. It is important to watch for signs of worsening asthma, such as increasing use of inhaled, short-acting beta2-adrenergic agonists or a significant decrease in peak expiratory flow (PEF) or lung function. Such findings require immediate evaluation. Patients should be advised to seek immediate attention should their condition deteriorate. Increasing the daily dosage of FORADIL AEROLIZER beyond the recommended dose in this situation is not appropriate. FORADIL AEROLIZER should not be used more frequently than twice daily (morning and evening) at the recommended dose.

Use of Anti-inflammatory Agents

There are no data demonstrating that FORADIL has any clinical anti-inflammatory effect and therefore it cannot be expected to take the place of corticosteroids. Patients who require oral or inhaled corticosteroids for treatment of asthma should be continued on this type of treatment even if they feel better as a result of initiating FORADIL AEROLIZER. Any change in corticosteroid dosage, in particular a reduction, should be made ONLY after clinical evaluation (see PRECAUTIONS, Information for Patients).

Cardiovascular Effects

Formoterol fumarate, like other beta2-agonists, can produce a clinically significant cardiovascular effect in some patients as measured by increases in pulse rate, blood pressure, and/or symptoms. Although such effects are uncommon after administration of FORADIL AEROLIZER at recommended doses, if they occur, the drug may need to be discontinued. In addition, beta-agonists have been reported to produce ECG changes, such as flattening of the T wave, prolongation of the QTc interval, and ST segment depression. The clinical significance of these findings is unknown. Therefore, formoterol fumarate, like other sympathomimetic amines, should be used with caution in patients with cardiovascular disorders, especially coronary insufficiency, cardiac arrhythmias, and hypertension (see PRECAUTIONS, General).

Immediate hypersensitivity reactions may occur after administration of FORADIL AEROLIZER, as demonstrated by cases of anaphylactic reactions, urticaria, angioedema, rash, and bronchospasm.

Do Not Exceed Recommended Dose

Fatalities have been reported in association with excessive use of inhaled sympathomimetic drugs in patients with asthma. The exact cause of death is unknown, but cardiac arrest following an unexpected development of a severe acute asthmatic crisis and subsequent hypoxia is suspected. In addition, data from clinical trials with FORADIL AEROLIZER suggest that the use of doses higher than recommended is associated with an increased risk of serious asthma exacerbations (see ADVERSE REACTIONS).

PRECAUTIONS

General

FORADIL AEROLIZER should not be used to treat acute symptoms of asthma. FORADIL AEROLIZER has not been studied in the relief of acute asthma symptoms and extra doses should not be used for that purpose. When prescribing FORADIL AEROLIZER, the physician should also provide the patient with an inhaled, short-acting beta2-agonist for treatment of symptoms that occur acutely, despite regular twice-daily (morning and evening) use of FORADIL AEROLIZER. Patients should also be cautioned that increasing inhaled beta2-agonist use is a signal of deteriorating asthma. (See Information for Patients and the accompanying Medication Guide.)

Formoterol fumarate, like other sympathomimetic amines, should be used with caution in patients with cardiovascular disorders, especially coronary insufficiency, cardiac arrhythmias, and hypertension; in patients with convulsive disorders or thyrotoxicosis; and in patients who are unusually responsive to sympathomimetic amines. Clinically significant changes in systolic and/or diastolic blood pressure, pulse rate and electrocardiograms have been seen infrequently in individual patients in controlled clinical studies with formoterol. Doses of the related beta2-agonist albuterol, when administered intravenously, have been reported to aggravate preexisting diabetes mellitus and ketoacidosis.

Beta-agonist medications may produce significant hypokalemia in some patients, possibly through intracellular shunting, which has the potential to produce adverse cardiovascular effects. The decrease in serum potassium is usually transient, not requiring supplementation.

Clinically significant changes in blood glucose and/or serum potassium were infrequent during clinical studies with long-term administration of FORADIL AEROLIZER at the recommended dose.

FORADIL AEROLIZER contains lactose, which contains trace levels of milk proteins. Allergic reactions to products containing milk proteins may occur in patients with severe milk protein allergy.

FORADIL capsules should ONLY be used with the AEROLIZER Inhaler and SHOULD NOT be taken orally.

FORADIL capsules should always be stored in the blister, and only removed IMMEDIATELY before use.

Information for Patients

Patients should be instructed to read the accompanying Medication Guide with each new prescription and refill. The complete text of the Medication Guide is reprinted at the end of this document. Patients should be given the following information:

1. Patients should be informed that long-acting beta 2-adrenergic agonists (LABA), including formoterol, the active ingredient in FORADIL AEROLIZER, increase the risk of asthma-related death and may increase the risk of asthma-related hospitalizations in pediatric and adolescent patients. Currently available data are inadequate to determine whether concurrent use of inhaled corticosteroids or other long-term asthma control drugs mitigates the increased risk of asthma- related death from LABA. Patients should be informed that FORADIL AEROLIZER should not be the only therapy for the treatment of asthma and must only be used as additional therapy when a long-term asthma control medication (e.g., inhaled corticosteroids) do not adequately control asthma symptoms. Patients should be informed that when FORADIL AEROLIZER is added to their treatment regimen they must continue to use their long-term asthma control medication.
2. FORADIL AEROLIZER is not indicated to relieve acute asthma symptoms and extra doses should not be used for that purpose. Acute symptoms should be treated with an inhaled, short-acting, beta2-agonist (the health-care provider should prescribe the patient with such medication and instruct the patient in how it should be used). Patients should be instructed to seek medical attention if their symptoms worsen, if FORADIL AEROLIZER treatment becomes less effective, or if they need more inhalations of a short-acting beta2-agonist than usual. Patients should not inhale more than the contents of one capsule at any one time. The daily dosage of FORADIL AEROLIZER should not exceed one capsule twice daily (24 mcg total daily dose).
3. FORADIL AEROLIZER should not be used as a substitute for oral or inhaled corticosteroids. The dosage of these medications should not be changed and they should not be stopped without consulting the physician, even if the patient feels better after initiating treatment with FORADIL AEROLIZER.
4. The active ingredient of FORADIL (formoterol fumarate) is a long-acting, bronchodilator used for the treatment of asthma, including nocturnal asthma, and for the prevention of exercise-induced bronchospasm. FORADIL AEROLIZER provides bronchodilation for up to 12 hours. Patients should be advised not to increase the dose or frequency of FORADIL AEROLIZER without consulting the prescribing physician. Patients should be warned not to stop or reduce concomitant asthma therapy without medical advice.
5. When FORADIL AEROLIZER is used for the prevention of EIB, the contents of one capsule should be taken at least 15 minutes prior to exercise. Additional doses of FORADIL AEROLIZER should not be used for 12 hours. Prevention of EIB has not been studied in patients who are receiving chronic FORADIL AEROLIZER administration twice daily and these patients should not use additional FORADIL AEROLIZER for prevention of EIB.
6. Patients should be informed that treatment with beta2-agonists may lead to adverse events which include palpitations, chest pain, rapid heart rate, tremor or nervousness.
7. Patients should be informed never to use FORADIL AEROLIZER with a spacer and never to exhale into the device.
8. Patients should avoid exposing the FORADIL capsules to moisture and should handle the capsules with dry hands. The AEROLIZER Inhaler should never be washed and should be kept dry. The patient should always use the new AEROLIZER Inhaler that comes with each refill.
9. Women should be advised to contact their physician if they become pregnant or if they are nursing.
10. Patients should be told that in rare cases, the gelatin capsule might break into small pieces. These pieces should be retained by the screen built into the AEROLIZER Inhaler. However, it remains possible that rarely, tiny pieces of gelatin might reach the mouth or throat after inhalation. The capsule is less likely to shatter when pierced if: storage conditions are strictly followed, capsules are removed from the blister immediately before use, and the capsules are only pierced once.
11. It is important that patients understand how to use the AEROLIZER Inhaler appropriately and how it should be used in relation to other asthma medications they are taking (see the accompanying Medication Guide).

Drug Interactions

If additional adrenergic drugs are to be administered by any route, they should be used with caution because the pharmacologically predictable sympathetic effects of formoterol may be potentiated.

Concomitant treatment with xanthine derivatives, steroids, or diuretics may potentiate any hypokalemic effect of adrenergic agonists.

The ECG changes and/or hypokalemia that may result from the administration of non-potassium sparing diuretics (such as loop or thiazide diuretics) can be acutely worsened by beta-agonists, especially when the recommended dose of the beta-agonist is exceeded. Although the clinical significance of these effects is not known, caution is advised in the co-administration of beta-agonist with non-potassium sparing diuretics.

Formoterol, as with other beta2-agonists, should be administered with extreme caution to patients being treated with monamine oxidase inhibitors, tricyclic antidepressants, or drugs known to prolong the QTc interval because the action of adrenergic agonists on the cardiovascular system may be potentiated by these agents. Drugs that are known to prolong the QTc interval have an increased risk of ventricular arrhythmias.

Beta-adrenergic receptor antagonists (beta-blockers) and formoterol may inhibit the effect of each other when administered concurrently. Beta-blockers not only block the therapeutic effects of beta2-agonists, such as formoterol, but may produce severe bronchospasm in asthmatic patients. Therefore, patients with asthma should not normally be treated with beta-blockers. However, under certain circumstances, e.g., as prophylaxis after myocardial infarction, there may be no acceptable alternatives to the use of beta-blockers in patients with asthma. In this setting, cardioselective beta-blockers could be considered, although they should be administered with caution.

Carcinogenesis, Mutagenesis, Impairment of Fertility

The carcinogenic potential of formoterol fumarate has been evaluated in 2-year drinking water and dietary studies in both rats and mice. In rats, the incidence of ovarian leiomyomas was increased at doses of 15 mg/kg and above in the drinking water study and at 20 mg/kg in the dietary study, but not at dietary doses up to 5 mg/kg (AUC exposure approximately 450 times human exposure at the maximum recommended daily inhalation dose). In the dietary study, the incidence of benign ovarian theca-cell tumors was increased at doses of 0.5 mg/kg and above (AUC exposure at the low dose of 0.5 mg/kg was approximately 45 times human exposure at the maximum recommended daily inhalation dose). This finding was not observed in the drinking water study, nor was it seen in mice (see below).

In mice, the incidence of adrenal subcapsular adenomas and carcinomas was increased in males at doses of 69 mg/kg and above in the drinking water study, but not at doses up to 50 mg/kg (AUC exposure approximately 590 times human exposure at the maximum recommended daily inhalation dose) in the dietary study. The incidence of hepatocarcinomas was increased in the dietary study at doses of 20 and 50 mg/kg in females and 50 mg/kg in males, but not at doses up to 5 mg/kg in either males or females (AUC exposure approximately 60 times human exposure at the maximum recommended daily inhalation dose). Also in the dietary study, the incidence of uterine leiomyomas and leiomyosarcomas was increased at doses of 2 mg/kg and above (AUC exposure at the low dose of 2 mg/kg was approximately 25 times human exposure at the maximum recommended daily inhalation dose). Increases in leiomyomas of the rodent female genital tract have been similarly demonstrated with other beta-agonist drugs.

Formoterol fumarate was not mutagenic or clastogenic in the following tests: mutagenicity tests in bacterial and mammalian cells, chromosomal analyses in mammalian cells, unscheduled DNA synthesis repair tests in rat hepatocytes and human fibroblasts, transformation assay in mammalian fibroblasts and micronucleus tests in mice and rats.

Reproduction studies in rats revealed no impairment of fertility at oral doses up to 3 mg/kg (approximately 1000 times the maximum recommended daily inhalation dose in humans on a mg/m2 basis).

Pregnancy, Teratogenic Effects, Pregnancy Category C

Formoterol fumarate has been shown to cause stillbirth and neonatal mortality at oral doses of 6 mg/kg (approximately 2000 times the maximum recommended daily inhalation dose in humans on a mg/m^2 basis) and above in rats receiving the drug during the late stage of pregnancy. These effects, however, were not produced at a dose of 0.2 mg/kg (approximately 70 times the maximum recommended daily inhalation dose in humans on a mg/m^2 basis). When given to rats throughout organogenesis, oral doses of 0.2 mg/kg and above delayed ossification of the fetus, and doses of 6 mg/kg and above decreased fetal weight. Formoterol fumarate did not cause malformations in rats or rabbits following oral administration. Because there are no adequate and well-controlled studies in pregnant women, FORADIL AEROLIZER should be used during pregnancy only if the potential benefit justifies the potential risk to the fetus.

Use in Labor and Delivery

Formoterol fumarate has been shown to cause stillbirth and neonatal mortality at oral doses of 6 mg/kg (approximately 2000 times the maximum recommended daily inhalation dose in humans on a mg/m^2 basis) and above in rats receiving the drug for several days at the end of pregnancy. These effects were not produced at a dose of 0.2 mg/kg (approximately 70 times the maximum recommended daily inhalation dose in humans on a mg/m^2 basis). There are no adequate and well-controlled human studies that have investigated the effects of FORADIL AEROLIZER during labor and delivery.

Because beta-agonists may potentially interfere with uterine contractility, FORADIL AEROLIZER should be used during labor only if the potential benefit justifies the potential risk.

Nursing Mothers

In reproductive studies in rats, formoterol was excreted in the milk. It is not known whether formoterol is excreted in human milk, but because many drugs are excreted in human milk, caution should be exercised if FORADIL AEROLIZER is administered to nursing women. There are no well-controlled human studies of the use of FORADIL AEROLIZER in nursing mothers.

Pediatric Use

Asthma

Available data from controlled clinical trials suggest that LABA increase the risk of asthma-related hospitalization in pediatric and adolescent patients. For pediatric and adolescent patients with asthma who require addition of a LABA to an inhaled corticosteroid, a fixed-dose combination product containing both an inhaled corticosteroid and LABA should ordinarily be used to ensure adherence with both drugs (see INDICATIONS AND USAGE and WARNINGS).

A total of 776 children 5 years of age and older with asthma were studied in three multiple-dose controlled clinical trials. Of the 512 children who received formoterol, 508 were 5-12 years of age, and approximately one third were 5-8 years of age.

Exercise-Induced Bronchospasm

A total of 25 pediatric patients, 4-11 years of age, were studied in two well-controlled single-dose clinical trials.

The safety and effectiveness of FORADIL AEROLIZER in pediatric patients below 5 years of age has not been established. (See CLINICAL TRIALS, Pediatric Asthma Trial, and ADVERSE REACTIONS, Experience in Pediatric, Adolescent and Adult Patients.)

Geriatric Use

Of the total number of patients who received FORADIL AEROLIZER in adolescent and adult chronic dosing asthma clinical trials, 318 were 65 years of age or older and 39 were 75 years of age and older. Of the 811 patients who received FORADIL AEROLIZER in two pivotal multiple-dose controlled clinical studies in patients with COPD, 395 (48.7%) were 65 years of age or older while 62 (7.6%) were 75 years of age or older. No overall differences in safety or effectiveness were observed between these subjects and younger subjects. A slightly higher frequency of chest infection was reported in the 39 asthma patients 75 years of age and older, although a causal relationship with FORADIL has not been established. Other reported clinical experience has not identified differences in responses between the elderly and younger adult patients, but greater sensitivity of some older individuals cannot be ruled out. (See PRECAUTIONS, Drug Interactions.)

ADVERSE REACTIONS

Long-acting beta 2-adrenergic agonists (LABA), including formoterol, the active ingredient in FORADIL AEROLIZER, increase the risk of asthma-related death and may increase the risk of asthma-related hospitalizations in pediatric and adolescent patients. Clinical trials with FORADIL AEROLIZER suggested a higher incidence of serious asthma exacerbations in patients who received FORADIL AEROLIZER than in those who received placebo. (See WARNINGS)

Experience in Pediatric, Adolescent and Adult Patients with Asthma

Of the 5,824 patients in multiple-dose controlled clinical trials, 1,985 were treated with FORADIL AEROLIZER at the recommended dose of 12 mcg twice daily. The following table shows adverse events where the frequency was greater than or equal to 1% in the FORADIL twice daily group and where the rates in the FORADIL group exceeded placebo. Three adverse events showed dose ordering among tested doses of 6, 12 and 24 mcg administered twice daily; tremor, dizziness and dysphonia.

NUMBER AND FREQUENCY OF ADVERSE EXPERIENCES IN PATIENTS 5 YEARS OF AGE AND OLDER FROM MULTIPLE-DOSE CONTROLLED CLINICAL TRIALS
Adverse Event | FORADIL AEROLIZER 12 mcg twice daily |  | Placebo
 | n | (%) | n | (%)
Total Patients | 1985 | (100) | 969 | (100)
Infection viral | 341 | (17.2) | 166 | (17.1)
Bronchitis | 92 | (4.6) | 42 | (4.3)
Chest infection | 54 | (2.7) | 4 | (0.4)
Dyspnea | 42 | (2.1) | 16 | (1.7)
Chest pain | 37 | (1.9) | 13 | (1.3)
Tremor | 37 | (1.9) | 4 | (0.4)
Dizziness | 31 | (1.6) | 15 | (1.5)
Insomnia | 29 | (1.5) | 8 | (0.8)
Tonsillitis | 23 | (1.2) | 7 | (0.7)
Rash | 22 | (1.1) | 7 | (0.7)
Dysphonia | 19 | (1.0) | 9 | (0.9)

In two 12-week controlled trials with combined enrollment of 1095 patients 12 years of age and older, FORADIL AEROLIZER 12 mcg twice daily was compared to FORADIL AEROLIZER 24 mcg twice daily, albuterol 180 mcg four times daily, and placebo. Serious asthma exacerbations (acute worsening of asthma resulting in hospitalization) occurred more commonly with FORADIL AEROLIZER 24 mcg twice daily than with the recommended dose of FORADIL AEROLIZER 12 mcg twice daily, albuterol, or placebo. The results are shown in the following table.

NUMBER AND FREQUENCY OF SERIOUS ASTHMA EXACERBATIONS IN PATIENTS 12 YEARS OF AGE AND OLDER FROM TWO 12-WEEK CONTROLLED CLINICAL TRIALS
 | Foradil 12 mcg twice daily | Foradil 24 mcg twice daily | Albuterol 180 mcg four times daily | Placebo
Trial #1
Serious asthma exacerbations | 0/136 (0) | 4/135 (3.0%)^1 | 2/134 (1.5%) | 0/136 (0)
Trial #2
Serious asthma exacerbations | 1/139 (0.7%) | 5/136 (3.7%)^2 | 0/138 (0) | 2/141 (1.4%)
^1 1 patient required intubation
^2 2 patients had respiratory arrest; 1 of the patients died

In a 16-week, randomized, multi-center, double-blind, parallel-group trial, patients who received either 24 mcg twice daily or 12 mcg twice daily doses of FORADIL AEROLIZER experienced more serious asthma exacerbations than patients who received placebo (see CLINICAL TRIALS). The results are shown in the following table.

NUMBER AND FREQUENCY OF SERIOUS ASTHMA EXACERBATIONS IN PATIENTS 12 YEARS OF AGE AND OLDER FROM A 16-WEEK TRIAL
 | Foradil 12 mcg twice daily | Foradil 24 mcg twice daily | Placebo
Serious asthma exacerbations | 3/527 (0.6%) | 2/527 (0.4%) | 1/514 (0.2%)

Experience in Children with Asthma

The safety of FORADIL AEROLIZER 12 mcg twice daily compared to FORADIL AEROLIZER 24 mcg twice daily and placebo was investigated in one large, multicenter, randomized, double-blind, 52-week clinical trial in 518 children with asthma (ages 5-12 years) in need of daily bronchodilators and anti-inflammatory treatment. More children who received FORADIL AEROLIZER 24 mcg twice daily than children who received FORADIL AEROLIZER 12 mcg twice daily or placebo experienced serious asthma exacerbations, as shown in the next table.

NUMBER AND FREQUENCY OF SERIOUS ASTHMA EXACERBATIONS IN PATIENTS 5-12 YEARS OF AGE FROM A 52-WEEK TRIAL
 | Foradil 12 mcg twice daily | Foradil 24 mcg twice daily | Placebo
Serious asthma exacerbations | 8/171 (4.7%) | 11/171 (6.4%) | 0/176 (0)

The numbers and percent of patients who reported adverse events were comparable in the 12 mcg twice daily and placebo groups. In general, the pattern of the adverse events observed in children differed from the usual pattern seen in adults. The adverse events that were more frequent in the formoterol group than in the placebo group reflected infection/inflammation (viral infection, rhinitis, tonsillitis, gastroenteritis) or abdominal complaints (abdominal pain, nausea, dyspepsia).

Experience in Adult Patients with COPD

Of the 1634 patients in two pivotal multiple-dose Chronic Obstructive Pulmonary Disease (COPD) controlled trials, 405 were treated with FORADIL AEROLIZER 12 mcg twice daily. The numbers and percent of patients who reported adverse events were comparable in the 12 mcg twice daily and placebo groups. Adverse events (AE's) experienced were similar to those seen in asthmatic patients, but with a higher incidence of COPD-related AE's in both placebo and formoterol treated patients.

The following table shows adverse events where the frequency was greater than or equal to 1% in the FORADIL AEROLIZER group and where the rates in the FORADIL AEROLIZER group exceeded placebo. The two clinical trials included doses of 12 mcg and 24 mcg, administered twice daily. Seven adverse events showed dose ordering among tested doses of 12 and 24 mcg administered twice daily; pharyngitis, fever, muscle cramps, increased sputum, dysphonia, myalgia, and tremor.

NUMBER AND FREQUENCY OF ADVERSE EXPERIENCES IN ADULT COPD PATIENTS TREATED IN MULTIPLE-DOSE CONTROLLED CLINICAL TRIALS
Adverse Event | FORADIL AEROLIZER 12 mcg twice daily |  | Placebo
 | n | (%) | n | (%)
Total patients | 405 | (100) | 420 | (100)
Upper respiratory tract infection | 30 | (7.4) | 24 | (5.7)
Pain back | 17 | (4.2) | 17 | (4.0)
Pharyngitis | 14 | (3.5) | 10 | (2.4)
Pain chest | 13 | (3.2) | 9 | (2.1)
Sinusitis | 11 | (2.7) | 7 | (1.7)
Fever | 9 | (2.2) | 6 | (1.4)
Cramps leg | 7 | (1.7) | 2 | (0.5)
Cramps muscle | 7 | (1.7) | 0
Anxiety | 6 | (1.5) | 5 | (1.2)
Pruritus | 6 | (1.5) | 4 | (1.0)
Sputum increased | 6 | (1.5) | 5 | (1.2)
Mouth dry | 5 | (1.2) | 4 | (1.0)

Overall, the frequency of all cardiovascular adverse events in the two pivotal studies was low and comparable to placebo (6.4% for FORADIL AEROLIZER 12 mcg twice daily, and 6.0% for placebo). There were no frequently-occurring specific cardiovascular adverse events for FORADIL AEROLIZER (frequency greater than or equal to 1% and greater than placebo).

Other adverse reactions to FORADIL AEROLIZER are similar in nature to other selective beta2-adrenoceptor agonists; e.g., angina, hypertension or hypotension, tachycardia, arrhythmias, nervousness, headache, tremor, dry mouth, palpitation, muscle cramps, nausea, dizziness, fatigue, malaise, hypokalemia, hyperglycemia, metabolic acidosis and insomnia.

Post Marketing Experience

In extensive worldwide marketing experience with FORADIL, serious exacerbations of asthma, including some that have been fatal, have been reported. While most of these cases have been in patients with severe or acutely deteriorating asthma (see WARNINGS), a few have occurred in patients with less severe asthma. It is not possible to determine from these individual case reports whether FORADIL AEROLIZER contributed to the events.

Rare reports of anaphylactic reactions, including severe hypotension and angioedema, have also been received in association with the use of formoterol fumarate inhalation powder.

DRUG ABUSE AND DEPENDENCE

There was no evidence in clinical trials of drug dependence with the use of FORADIL.

OVERDOSAGE

The expected signs and symptoms with overdosage of FORADIL AEROLIZER are those of excessive beta-adrenergic stimulation and/or occurrence or exaggeration of any of the signs and symptoms listed under ADVERSE REACTIONS, e.g., angina, hypertension or hypotension, tachycardia, with rates up to 200 beats/min., arrhythmias, nervousness, headache, tremor, seizures, muscle cramps, dry mouth, palpitation, nausea, dizziness, fatigue, malaise, hypokalemia, hyperglycemia, and insomnia. Metabolic acidosis may also occur. As with all inhaled sympathomimetic medications, cardiac arrest and even death may be associated with an overdose of FORADIL AEROLIZER.

Treatment of overdosage consists of discontinuation of FORADIL AEROLIZER together with institution of appropriate symptomatic and/or supportive therapy. The judicious use of a cardioselective beta-receptor blocker may be considered, bearing in mind that such medication can produce bronchospasm. There is insufficient evidence to determine if dialysis is beneficial for overdosage of FORADIL AEROLIZER. Cardiac monitoring is recommended in cases of overdosage.

The minimum acute lethal inhalation dose of formoterol fumarate in rats is 156 mg/kg (approximately 53,000 and 25,000 times the maximum recommended daily inhalation dose in adults and children, respectively, on a mg/m^2 basis). The median lethal oral doses in Chinese hamsters, rats, and mice provide even higher multiples of the maximum recommended daily inhalation dose in humans.

DOSAGE AND ADMINISTRATION

FORADIL capsules should be administered only by the oral inhalation route and only using the AEROLIZER Inhaler (see the accompanying Medication Guide). FORADIL capsules should not be ingested (i.e., swallowed) orally. FORADIL capsules should always be stored in the blister, and only removed IMMEDIATELY BEFORE USE.

Treatment of Asthma

Long-acting beta2-adrenergic agonists (LABA), such as formoterol, the active ingredient in FORADIL AEROLIZER, increase the risk of asthma-related death (see Warnings). Because of this risk, use of FORADIL AEROLIZER for the treatment of asthma without concomitant use of a long-term asthma control medication, such as an inhaled corticosteroid, is contraindicated. Use FORADIL AEROLIZER only as additional therapy for patients with asthma who are currently taking but are inadequately controlled on a long-term asthma control medication, such as an inhaled corticosteroid. Once asthma control is achieved and maintained, assess the patient at regular intervals and step down therapy (e.g. discontinue FORADIL AEROLIZER) if possible without loss of asthma control, and maintain the patient on a long-term asthma control medication, such as an inhaled corticosteroid. Do not use FORADIL AEROLIZER for patients whose asthma is adequately controlled on low or medium dose inhaled corticosteroids.

Pediatric and Adolescent Patients

Available data from controlled clinical trials suggest that LABA increase the risk of asthma-related hospitalization in pediatric and adolescent patients. For patients with asthma less than 18 years of age who require addition of a LABA to an inhaled corticosteroid, a fixed-dose combination product containing both an inhaled corticosteroid and LABA should ordinarily be used to ensure adherence with both drugs. In cases where use of a separate long-term asthma control medication (e.g. inhaled corticosteroid) and LABA is clinically indicated, appropriate steps must be taken to ensure adherence with both treatment components. If adherence cannot be assured, a fixed-dose combination product containing both an inhaled corticosteroid and LABA is recommended.

For adults and children 5 years of age and older, the usual dosage is the inhalation of the contents of one 12-mcg FORADIL capsule every 12 hours using the AEROLIZER Inhaler. The patient must not exhale into the device. The total daily dose of FORADIL should not exceed one capsule twice daily (24 mcg total daily dose). More frequent administration or administration of a larger number of inhalations is not recommended. If symptoms arise between doses, an inhaled short-acting beta2-agonist should be taken for immediate relief.

If a previously effective dosage regimen fails to provide the usual response, medical advice should be sought immediately as this is often a sign of destabilization of asthma. Under these circumstances, the therapeutic regimen should be re-evaluated.

For Prevention of Exercise-Induced Bronchospasm (EIB)

Use of FORADIL AEROLIZER as a single agent for the prevention of exercise-induced bronchospasm may be clinically indicated in patients who do not have persistent asthma. In patients with persistent asthma, use of FORADIL AEROLIZER for the prevention of exercise-induced bronchospasm may be clinically indicated, but the treatment of asthma should include a long-term asthma control medication, such as an inhaled corticosteroid. For adults and children 5 years of age or older, the usual dosage is the inhalation of the contents of one 12-mcg FORADIL capsule at least 15 minutes before exercise administered on an occasional as needed basis. When used intermittently as needed for prevention, protection may last up to 12 hours.

Additional doses of FORADIL AEROLIZER should not be used for 12 hours after the administration of this drug. Regular, twice-daily dosing has not been studied in preventing EIB. Patients who are receiving FORADIL AEROLIZER twice daily for treatment of their asthma should not use additional doses for prevention of EIB and may require a short-acting bronchodilator.

For Maintenance Treatment of Chronic Obstructive Pulmonary Disease (COPD)

The usual dosage is the inhalation of the contents of one 12 mcg FORADIL capsule every 12 hours using the AEROLIZER inhaler.

A total daily dose of greater than 24 mcg is not recommended.

If a previously effective dosage regimen fails to provide the usual response, medical advice should be sought immediately as this is often a sign of destabilization of COPD. Under these circumstances, the therapeutic regimen should be re-evaluated and additional therapeutic options should be considered.

HOW SUPPLIED

FORADIL AEROLIZER contains: aluminum blister-packaged 12-mcg FORADIL (formoterol fumarate) clear gelatin capsules with "CG" printed on one end and "FXF" printed on the opposite end; one AEROLIZER Inhaler; and Medication Guide.

Unit Dose (blister pack)

Box of 60 (strips of 6). . . . . . . . . . . . . . . . . . . . . . . . . . NDC 54868-4972-1

FORADIL capsules should be used with the AEROLIZER Inhaler only. The AEROLIZER Inhaler should not be used with any other capsules.

Prior to dispensing: Store in a refrigerator, 2°C-8°C (36°F-46°F)

After dispensing to patient: Store at 20°C to 25°C (68°F to 77°F) [see USP Controlled Room Temperature]. Protect from heat and moisture. CAPSULES SHOULD ALWAYS BE STORED IN THE BLISTER AND ONLY REMOVED FROM THE BLISTER IMMEDIATELY BEFORE USE.

Always discard the FORADIL capsules and AEROLIZER Inhaler by the "Use by" date and always use the new AEROLIZER Inhaler provided with each new prescription.

Keep out of the reach of children.

Manufactured by:

Novartis Pharma AG, Basle, Switzerland

Distributed by:

Schering Corporation, a subsidiary of

MERCK & CO., INC.

Whitehouse Station, NJ 08889, USA

Copyright © 2011 Schering Corp.,

a subsidiary of MERCK & CO., INC.

All rights reserved.

May 2011

Additional barcode labeling by:

Physicians Total Care, Inc.

Tulsa, Oklahoma 74146

Medication Guide

Foradil® [FOR-a-dil] Aerolizer®

(formoterol fumarate inhalation powder)

Important: Do not swallow FORADIL capsules. FORADIL capsules are used only with the Aerolizer inhaler that comes with FORADIL AEROLIZER. Never place a capsule in the mouthpiece of the AEROLIZER Inhaler.

Read the Medication Guide that comes with FORADIL AEROLIZER before you start using it and each time you get a refill. There may be new information. This Medication Guide does not take the place of talking to your health care provider about your medical condition or treatment.

What is the most important information I should know about FORADIL AEROLIZER?

FORADIL AEROLIZER can cause serious side effects, including:

1. People with asthma who take long-acting beta2-adrenergic agonist (LABA) medicines, such as formoterol fumarate inhalation powder (FORADIL AEROLIZER), have an increased risk of death from asthma problems.

- Call your healthcare provider if breathing problems worsen over time while using FORADIL AEROLIZER. You may need a different treatment.
- Get emergency medical care if:
  - breathing problems worsen quickly, and
  - you use your rescue inhaler medicine, but it does not relieve your breathing problems.

2. Do not use FORADIL AEROLIZER as your only asthma medicine. FORADIL AEROLIZER must only be used with a long-term asthma control medicine, such as an inhaled corticosteroid.

3. When your asthma is well controlled, your healthcare provider may tell you to stop taking FORADIL AEROLIZER. Your healthcare provider will decide if you can stop FORADIL AEROLIZER without loss of asthma control. You will continue taking your long-term asthma control medicine, such as an inhaled corticosteroid.

4. Children and adolescents who take LABA medicines may have an increased risk of being

hospitalized for asthma problems.

What is FORADIL AEROLIZER?

FORADIL AEROLIZER is a long-acting beta2-agonist (LABA). LABA medicines help the muscles around the airways in your lungs stay relaxed to prevent asthma symptoms, such as wheezing and shortness of breath. These symptoms can happen when the muscles around the airways tighten. This makes it hard to breathe. In severe cases, wheezing can stop your breathing and cause death if not treated right away.

FORADIL AEROLIZER is used for asthma, exercise-induced bronchospasm (EIB) and chronic obstructive pulmonary disease (COPD) as follows:

Asthma

FORADIL AEROLIZER is used with a long-term asthma control medicine, such as an inhaled corticosteroid, in adults and children ages 5 and older:

- to control symptoms of asthma, and
- to prevent symptoms such as wheezing

LABA medicines, such as FORADIL AEROLIZER, increase the risk of death from asthma problems. FORADIL AEROLIZER is not for adults and children with asthma who are well controlled with long-term asthma control medicine, such as low to medium dose of an inhaled corticosteroid medicine.

Exercise-Induced Bronchospasm (EIB)

FORADIL AEROLIZER is used to prevent wheezing caused by exercise in adults and children 5 years of age and older.

- If you have EIB only, your healthcare provider may prescribe only FORADIL AEROLIZER for your condition
- If you have EIB and asthma, your healthcare provider should also prescribe a long-term asthma control medicine, such as an inhaled corticosteroid

Chronic Obstructive Pulmonary Disease (COPD)

FORADIL AEROLIZER is used long-term, 2 times each day (morning and evening), to control symptoms of COPD and prevent wheezing in adults with COPD.

Who should not use FORADIL AEROLIZER?

- Do not take FORADIL AEROLIZER to treat your asthma without a long-term asthma control medicine, such as an inhaled corticosteroid.
- If you are allergic to formoterol fumarate or any of the ingredients in FORADIL AEROLIZER. Ask your healthcare provider if you are not sure. See the end of this Medication Guide for a complete list of ingredients in FORADIL AEROLIZER.

What should I tell my healthcare provider before using FORADIL AEROLIZER?

Tell your healthcare provider about all of your health conditions, including if you:

- have heart problems
- have high blood pressure
- have seizures
- have thyroid problems
- have diabetes
- are pregnant or planning to become pregnant. It is not known if FORADIL AEROLIZER may harm your unborn baby.
- are breastfeeding. It is not known if FORADIL AEROLIZER passes into your milk and if it can harm your baby.
- are allergic to FORADIL AEROLIZER, any other medicines, or food products.

FORADIL AEROLIZER contains lactose (milk sugar) and a small amount of milk proteins. It is possible that allergic reactions may happen in patients who have a severe milk protein allergy.

Tell your healthcare provider about all the medicines you take including prescription and non-prescription medicines, vitamins, and herbal supplements. FORADIL AEROLIZER and certain other medicines may interact with each other. This may cause serious side effects.

Know the medicines you take. Keep a list and show it to your healthcare provider and pharmacist each time you get a new medicine.

How do I use FORADIL capsules with the Aerolizer inhaler?

See the step-by-step instructions for using FORADIL Capsules with the Aerolizer inhaler at the end of this Medication Guide. Do not use FORADIL unless your healthcare provider has taught you and you understand everything. Ask your healthcare provider or pharmacist if you have any questions.

- Children should use FORADIL AEROLIZER with an adult’s help, as instructed by the child’s healthcare provider.
- Use FORADIL AEROLIZER exactly as prescribed. Do not use FORADIL AEROLIZER more often than prescribed.
- For asthma and COPD, the usual dose is 1 FORADIL capsule inhaled through the AEROLIZER inhaler 2 times each day (morning and evening). The 2 doses should be about 12 hours apart.
- For preventing exercise-induced bronchospasm, the usual dose is 1 FORADIL capsule inhaled through the AEROLIZER inhaler at least 15 minutes before exercise, as needed. Do not use FORADIL AEROLIZER more often than every 12 hours. Do not use extra FORADIL AEROLIZER before exercise if you already use it 2 times each day.
- If you miss a dose of FORADIL AEROLIZER, just skip that dose. Take your next dose at your usual time. Never take 2 doses at one time.
- Do not use a spacer device with FORADIL AEROLIZER.
- Do not breathe into FORADIL AEROLIZER.
- While you are using FORADIL AEROLIZER 2 times each day, do not use other medicines that contain a long-acting beta2-agonist (LABA) for any reason. Ask your healthcare provider or pharmacist for a list of these medicines.
- Do not stop using FORADIL AEROLIZER or any of your asthma medicines unless told to do so by your healthcare provider because your symptoms might get worse. Your healthcare provider will change your medicines as needed.
- FORADIL AEROLIZER does not relieve sudden symptoms. Always have a rescue inhaler medicine with you to treat sudden symptoms. If you do not have an inhaled, short-acting bronchodilator, contact your healthcare provider to have one prescribed for you.

- Call your healthcare provider or get medical care right away if:
  - your breathing problems worsen with FORADIL AEROLIZER
  - you need to use your rescue inhaler medicine more often than usual
  - your rescue inhaler medicine does not work as well for you at relieving symptoms
  - you need to use 4 or more inhalations of your rescue inhaler medicine for 2 or more days in a row
  - you use 1 whole canister of your rescue inhaler medicine in 8 weeks time
  - your peak flow meter results decrease. Your healthcare provider will tell you the numbers that are right for you.
  - you have asthma and your symptoms do not improve after using FORADIL AEROLIZER regularly for 1 week.

What are the possible side effects with FORADIL AEROLIZER?

FORADIL AEROLIZER may cause serious side effects, including:

- See “What is the most important information I should know about FORADIL AEROLIZER?”
- Bronchospasm with wheezing or coughing and difficulty breathing
- Low blood potassium (which may cause symptoms of muscle spasm, muscle weakness or abnormal heart rhythm)
- Fast or irregular heart beat (palpitations)
- Serious allergic reactions including rash, hives, swelling of the face, mouth, and tongue, and breathing problems. Call your healthcare provider or get emergency medical care if you get any symptoms of a serious allergic reaction.

Other possible side effects with FORADIL AEROLIZER include:

- chest pain
- increased blood pressure
- nervousness
- dry mouth
- muscle cramps
- nausea
- dizziness
- tiredness
- high blood sugar
- high blood acid
- trouble sleeping

Common side effects with FORADIL AEROLIZER include:

- headache
- tremor

Tell your healthcare provider about any side effect that bothers you or that does not go away.

These are not all the side effects with FORADIL AEROLIZER. Ask your healthcare provider or pharmacist for more information.

Call your doctor for medical advice about side effects. You may report side effects to FDA at 1-800-FDA-1088.

How do I store FORADIL AEROLIZER?

- Store FORADIL AEROLIZER at room temperature between 68° F and 77° F (20° C to 25° C). Protect FORADIL AEROLIZER from heat and moisture. Do not remove FORADIL capsules from their foil blister package until just before use.
- Always discard the old AEROLIZER inhaler by the “Use by” date and use the new one provided with each new prescription.
- Safely discard FORADIL capsules and the Aerolizer inhaler if no longer needed or is out-of-date.
- Keep FORADIL AEROLIZER and all medicines out of the reach of children.

General Information about FORADIL AEROLIZER

Medicines are sometimes prescribed for purposes other than those listed in a Medication Guide. Do not use FORADIL AEROLIZER for a condition for which it was not prescribed. Do not give FORADIL AEROLIZER to other people, even if they have the same condition. It may harm them.

This Medication Guide summarizes the most important information about FORADIL AEROLIZER. If you would like more information, talk with your healthcare provider. You can ask your healthcare provider or pharmacist for information about FORADIL AEROLIZER that was written for healthcare professionals. If you have any questions about the use of FORADIL AEROLIZER, call (toll-free) 1-800-526-4099 or go to www.foradil.us.

What are the ingredients in FORADIL AEROLIZER?

Active ingredient: formoterol fumarate

Inactive ingredients: lactose (contains milk proteins), gelatin (capsule shell)

Instructions for Using FORADIL AEROLIZER

Do not swallow FORADIL capsules.

Follow the instructions below for using your FORADIL AEROLIZER. You will breathe-in (inhale) the medicine in the FORADIL capsules from the FORADIL AEROLIZER. If you have any questions, ask your healthcare provider or pharmacist.

FORADIL AEROLIZER

- FORADIL AEROLIZER consists of FORADIL capsules and a AEROLIZER Inhaler.
- FORADIL capsules come on blister cards.
- Keep your FORADIL and AEROLIZER Inhaler dry. Handle with DRY hands.

Foil blister card

The Aerolizer consists of the following parts:
1. A cap to protect the mouthpiece of the base
2. A base that allows the proper release of medicine from the capsule. The base consists of:
3. A mouth piece
4. A capsule chamber
5. A button with “winglets” (projecting side pieces) and pins on each side
6. An air inlet channel.

With each new prescription of FORADIL AEROLIZER or refill, your pharmacist should have written the “Use by” date on the sticker on the outside of the FORADIL AEROLIZER box. Remove the “Use by” sticker on the box and place it on the AEROLIZER Inhaler cover that comes with FORADIL. If the sticker is blank, count 4 months from the date you got your FORADIL AEROLIZER from the pharmacy and write this date on the sticker. Also, check the expiration date stamped on the box. If this date is less than 4 months from your purchase date, write this date on the sticker.

Do not use FORADIL capsules with any other capsule inhaler, and do not use the AEROLIZER inhaler to take any other capsule medicine.

Taking a dose of FORADIL AEROLIZER requires the following steps:

1. Do not remove a FORADIL capsule from the blister card until you are ready for a dose.

2. Pull off the AEROLIZER Inhaler cover. (Figure 1)

Figure 1

3. Hold the base of the AEROLIZER Inhaler firmly and twist the mouthpiece in the direction of the arrow to open. (Figure 2) Push the buttons in on each side to make sure that you can see 4 pins in the capsule well of the AEROLIZER Inhaler.

Figure 2

4. Separate one FORADIL capsule blister by tearing at the pre-cut lines. (Figure 3)

Figure 3

5. Peel the paper backing that covers one FORADIL capsule on the blister card. Push the FORADIL capsule through the foil. (Figure 4)

Figure 4

6. Place the FORADIL capsule in the capsule-chamber in the base of the AEROLIZER Inhaler. Never place a capsule directly into the mouthpiece. (Figure 5)

Figure 5

7. Twist the mouthpiece back to the closed position. (Figure 6)

Figure 6

8. Hold the mouthpiece of the AEROLIZER Inhaler upright and press both buttons at the same time. Only press the buttons ONCE. You should hear a click as the FORADIL capsule is being pierced. (Figure 7)

Figure 7

9. Release the buttons. If the buttons stay stuck, grasp the wings on the buttons and pull them out of the stuck position before the next step. Do not push the buttons a second time. This may cause the FORADIL capsule to break into small pieces. There is a screen built into the AEROLIZER Inhaler to hold these small pieces. It is possible that tiny pieces of a FORADIL capsule might reach your mouth or throat when you inhale the medicine. This will not harm you, but to avoid this, only pierce the capsule once. The FORADIL capsules are also less likely to break into small pieces if you store them the right way (See “How do I store FORADIL AEROLIZER?”).

10. Breathe out (exhale) fully. Do not exhale into the AEROLIZER mouthpiece. (Figure 8)

Figure 8

11. Tilt your head back slightly. Keep the AEROLIZER Inhaler level, with the blue buttons to the left and right (not up and down). Place the mouthpiece in your mouth and close your lips around the mouthpiece. (Figures 9 and 10)

12. Breathe in quickly and deeply (Figure 11). This will cause the FORADIL capsule to spin around in the chamber and deliver your dose of medicine. You should hear a whirring noise and experience a sweet taste in your mouth. If you do not hear the whirring noise, the capsule may be stuck. If this occurs, open the AEROLIZER Inhaler and loosen the capsule allowing it to spin freely. Do not try to loosen the capsule by pressing the buttons again. (You will have to repeat steps 10 to 12 again to get your dose.)

Figure 11

13. Remove the AEROLIZER Inhaler from your mouth. Continue to hold your breath as long as you can and then exhale.

14. Open the AEROLIZER Inhaler to see if any powder is still in the capsule. If any powder remains in the capsule repeat steps 10 to 13. Most people are able to empty the capsule in one or two inhalations.

15. After use, open the AEROLIZER Inhaler, remove and discard the empty capsule. Do not leave a used capsule in the chamber.

16. Close the mouthpiece and replace the cover.

Remember:

- Never breathe into the AEROLIZER Inhaler.
- Never take the AEROLIZER Inhaler apart.
- Never place a FORADIL capsule directly into the mouthpiece of the AEROLIZER Inhaler.
- Never leave a used FORADIL capsule in the AEROLIZER Inhaler chamber.
- Always use the AEROLIZER Inhaler in a level position.
- Never wash the AEROLIZER Inhaler. Keep it dry.
- Always keep the AEROLIZER Inhaler and FORADIL capsules in a dry place.
- Always use the new AEROLIZER Inhaler that comes with your refill.

Manufactured by:

Novartis Pharma AG, Basle, Switzerland

Distributed by:

Schering Corporation, a subsidiary of

MERCK & CO., INC.

Whitehouse Station, NJ 08889, USA

Copyright © 2011 Schering Corp.,a subsidiary of MERCK & CO., INC.

All rights reserved.

FORADIL is a registered trademark of Astellas Pharma Inc.

AEROLIZER is a registered trademark of Novartis AG.

This Medication Guide has been approved by the U.S. Food and Drug Administration.

T2011-82

February 2011

Principal display panel

Package Label – 12 mcg per capsule

Rx Only NDC 54868-4972-1

Foradil® Aerolizer®

(formoterol fumarate inhalation powder)

FOR INHALATION USE ONLY

Foradil® capsules for use with Aerolizer® Inhaler only

60 Capsules